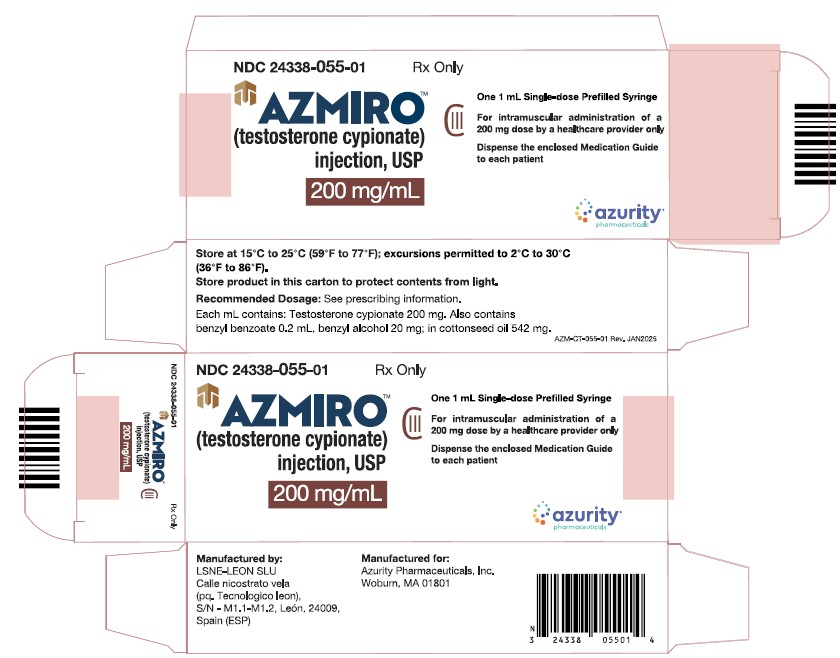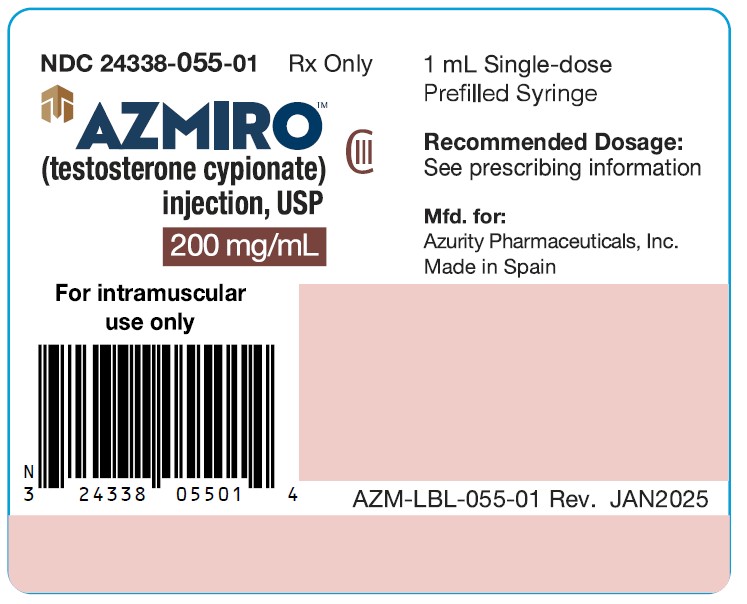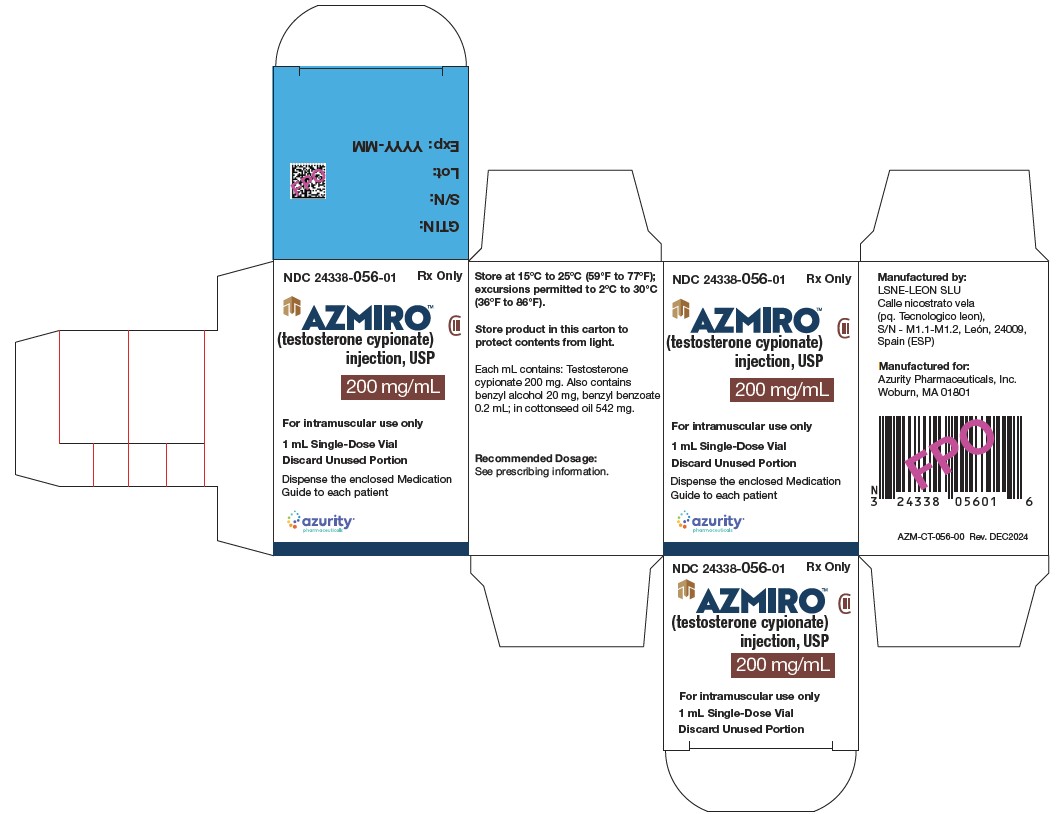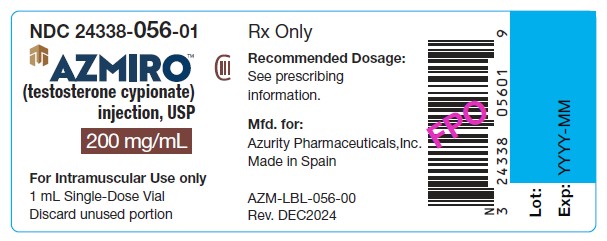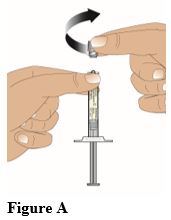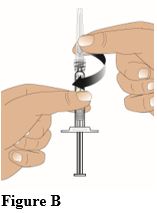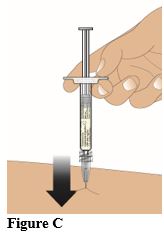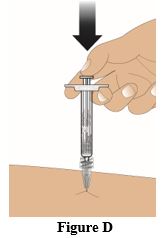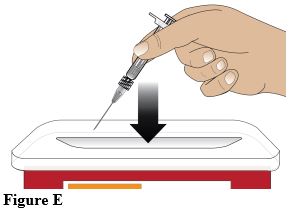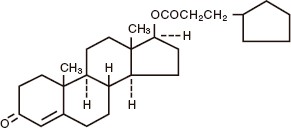 DRUG LABEL: AZMIRO
NDC: 24338-056 | Form: INJECTION, SOLUTION
Manufacturer: Azurity Pharmaceuticals, Inc.
Category: prescription | Type: Human Prescription Drug Label
Date: 20250725
DEA Schedule: CIII

ACTIVE INGREDIENTS: TESTOSTERONE CYPIONATE 200 mg/1 mL
INACTIVE INGREDIENTS: BENZYL BENZOATE 0.2 mL/1 mL; COTTONSEED OIL 542 mg/1 mL; BENZYL ALCOHOL 20 mg/1 mL

HIGHLIGHTS OF PRESCRIBING INFORMATION

These highlights do not include all the information needed to use AZMIRO safely and effectively. See full prescribing information for AZMIRO.
AZMIRO TM (testosterone cypionate) injection, for intramuscular use, CIII
Initial U.S. Approval: 1953

RECENT MAJOR CHANGES

Warnings and Precautions, Venous Thromboembolism (5.2) 07/2025
Warnings and Precautions, Blood Pressure Increases (5.4) 07/2025
Warnings and Precautions, Cardiovascular Risk (5.2) Removed 07/2025

1 INDICATIONS & USAGE

AZMIRO is an androgen indicated for testosterone replacement therapy in males for conditions associated with a deficiency or absence of endogenous testosterone (1):

Limitations of Use:
• Safety and efficacy of AZMIRO in men with “age-related hypogonadism” (also referred to as “late-onset hypogonadism”) have not been established (1).
• Safety and effectiveness in pediatric patients below the age of 12 years have not been established (8.4).

2 DOSAGE AND ADMINISTRATION

• Injectable testosterone products may have different doses, strengths, or administration instructions and they are not substitutable on a milligram-per-milligram basis. Administer AZMIRO by deep gluteal intramuscular injection only (2.1).
• Prior to initiating AZMIRO, confirm the diagnosis of hypogonadism by ensuring that serum testosterone concentrations have been measured in the morning on at least two separate days and that these serum concentrations are below the normal range (2.2).
• Recommended dosage is 50 mg to 400 mg administered every two to four weeks as a deep intramuscular injection in the gluteal muscle.
Individualize the dose and schedule based on the patient’s age, diagnosis, response to treatment, and the appearance of adverse reactions (2.3).

• The prefilled syringe should be administered as an intramuscular injection by a healthcare professional only.

3 DOSAGE FORMS & STRENGTHS

Injection: 200 mg/mL in a single-dose vial (3)

200 mg/mL in a single-dose prefilled syringe (3)

4 CONTRAINDICATIONS

• Known hypersensitivity to AZMIRO or any of its components, skin manifestations and anaphylactoid reactions have been reported (4)
• Men with carcinoma of the breast or known or suspected carcinoma of the prostate (4).
• Women who are pregnant. Testosterone may cause fetal harm (4).

5 WARNINGS AND PRECAUTIONS

• Polycythemia: Monitor hematocrit periodically during treatment. Discontinue AZMIRO, if necessary (5.1).
• Venous thromboembolism (VTE): VTE, including deep vein thrombosis (DVT) and pulmonary embolism (PE) have been reported in patients using testosterone products. Discontinue AZMIRO if VTE is suspected and initiate appropriate workup and management (5.2).
• Worsening of Benign Prostatic Hyperplasia (BPH) and Potential Risk of Prostate Cancer: Monitor patients with benign prostatic hyperplasia (BPH) for worsening of signs and symptoms of BPH. Evaluate patients for prostate cancer, including monitoring prostate specific antigen (PSA) prior to initiating and during treatment with androgens (5.3).

• Blood Pressure Increases: Testosterone can increase blood pressure, which can increase cardiovascular risk over time. Measure blood pressure periodically. Not recommended for use in men with uncontrolled hypertension (5.4)
• Abuse of Testosterone and Monitoring of Serum Testosterone: If testosterone use at doses higher than recommended for the approved indication and in combination with other anabolic androgenic steroids is suspected, check serum testosterone concentration (5.5)
• Potential for Adverse Effects on Spermatogenesis: AZMIRO may cause azoospermia (5.7, 8.3).
• Edema: Edema, with or without congestive heart failure (CHF), may occur in patients with pre-existing cardiac, renal, or hepatic disease. Discontinue AZMIRO and initiate appropriate workup (5.9).
• Sleep Apnea: AZMIRO may potentiate sleep apnea in those with risk factors (5.10).
• Lipid Changes: Testosterone may affect serum lipid profile. Monitor patient lipid concentrations; if necessary, adjust dosage of lipid lowering drug(s) or discontinue AZMIRO (5.12).
• Adverse Effects on Bone Maturation: Testosterone may result in acceleration of bone age and premature closure of epiphyses in pediatric patients which may result in compromised adult stature. Monitor the effect on bone maturation by assessing bone age of the wrist and hand every 6 months.

6 ADVERSE REACTIONS

Common adverse reactions (incidence ≥4%) are injection site erythema and injection site reaction (6.1).
Other adverse reactions include: polycythemia, gynecomastia, headache, and depression (6.2).
To report SUSPECTED ADVERSE REACTIONS, contact Azurity Pharmaceuticals, Inc. at 1-800-461-7449 or FDA at 1-800-FDA-1088 or www.fda.gov/medwatch.

7 DRUG INTERACTIONS

• Insulin: In patients with diabetes, concomitant use with AZMIRO may decrease blood glucose and insulin requirements (7.1).
• Oral Anticoagulants: Concomitant use with AZMIRO may cause changes in anticoagulant activity. Monitor International Normalized Ratio and prothrombin time frequently (7.2).
• Corticosteroids: Concomitant use with AZMIRO may result in increased fluid retention. Use with caution, particularly in patients with cardiac, renal, or hepatic disease (7.3).

8 USE IN SPECIFIC POPULATIONS

Geriatric Patients: Geriatric patients treated with androgens may also be at risk for worsening of signs and symptoms of BPH and prostatic carcinoma (8.5).

FULL PRESCRIBING INFORMATION

1 INDICATIONS & USAGE

AZMIRO is indicated for testosterone replacement therapy in males in conditions associated with a deficiency or absence of endogenous testosterone:
• Primary hypogonadism (congenital or acquired): testicular failure due to conditions such as cryptorchidism, bilateral torsion, orchitis, vanishing testis syndrome; or orchiectomy, Klinefelter’s syndrome, or toxic damage from alcohol or heavy metals, chemotherapy, or toxic damage from alcohol or heavy metals. These men usually have low serum testosterone concentrations and gonadotropins (follicle stimulating hormone (FSH), luteinizing hormone (LH)) above the normal range [ see Dosage and Administration (2.2) ].
• Hypogonadotropic hypogonadism (congenital or acquired): gonadotropin or luteinizing hormone-releasing hormone (LHRH) deficiency, or pituitary-hypothalamic injury from tumors, trauma, or radiation. These men have low testosterone serum concentrations but have gonadotropins in the normal or low range [ see Dosage and Administration (2.2)].
Limitations of Use
• Safety and efficacy of AZMIRO in men with “age- related hypogonadism” (also referred to as “late-onset hypogonadism”) have not been established.
• Safety and efficacy of AZMIRO in pediatric patients below the age of 12 years have not been established [ see Use in Specific Populations (8.4) ].

2 DOSAGE AND ADMINISTRATION

2.1 Important Dosage Information

• Injectable testosterone products may have different doses, strengths, or administration instructions and they are not substitutable on a milligram-per-milligram basis.
• Administer AZMIRO by deep gluteal intramuscular injection only.

2.2 Confirmation of Hypogonadism before Initiation of AZMIRO

Prior to initiating AZMIRO, confirm the diagnosis of hypogonadism by ensuring that serum testosterone concentrations have been measured in the morning on at least two separate days and that these serum testosterone concentrations are below the normal range.

2.3 Recommended Dosage

The recommended dosage of AZMIRO is 50 mg to 400 mg administered every two to four weeks as a deep intramuscular injection in the gluteal muscle.
Individualize the dose and schedule of AZMIRO based on the patient’s age, diagnosis, response to treatment, and the appearance of adverse reactions.

2.4 Administration Instructions for AZMIRO Single-dose Vial

• Visually inspect parenteral drug products for particulate matter and discoloration prior to administration, whenever solution and container permit.
• Discard any unused portions of drug remaining in the single-dose vial.

2.5 Important Administration Information and Administration Instructions for AZMIRO Prefilled Syringe

Important Administration Information
• The prefilled syringe should be administered as an intramuscular injection by a healthcare professional only.
• The prefilled syringe should only be used to administer doses of 200 mg. For administration of doses other than 200 mg, use the AZMIRO single-dose vial.
• AZMIRO 200 mg/mL is supplied as single-dose prefilled syringe with luer lock connector.
• The prefilled syringe carton does not contain a needle. Obtain suitable needle separately.
• Do not use if the packaging appears to be damaged.
• Do not use the prefilled syringe if it appears to be damaged or the syringe cap is detached from the Luer lock.
Administration Instructions
Hold the syringe upright while gripping the ribbed part of the luer lock. Then with the other hand unscrew the syringe cap in a counter-clockwise direction (Figure A). Once the syringe cap is removed, avoid any hand contact with the tip of the glass syringe, to maintain the sterility.

• Screw the needle onto the luer lock end of the syringe in a clockwise direction until it is firmly attached (Figure B).

• Remove the needle cap by pulling it straight off.
• Check syringe for air bubbles. If there are air bubbles: Gently tap the syringe with your fingers until the bubbles rise to the top of the syringe. Then press the plunger up to slowly expel the air.
• Clean the injection site for injection into the gluteal muscle with an alcohol swab and allow the skin to dry.
• Insert the needle straight into the skin at a 90° angle (Figure C). Push the plunger down to inject the entire contents (1 mL) of the prefilled syringe (Figure D).

• After administration of the injection, discard the syringe into a sharps disposal container or in accordance with local requirements (Figure E).

3 DOSAGE FORMS & STRENGTHS

Injection:
• 200 mg/mL available as 1 mL of clear colorless to pale yellow solution filled in a single-dose glass vial.
• 200 mg/mL available as 1 mL of clear colorless to pale yellow solution filled in a single-dose glass prefilled syringe.

4 CONTRAINDICATIONS

AZMIRO is contraindicated in:
• Known hypersensitivity to AZMIRO or to any of its components [see Description (11)]. Hypersensitivity, including skin manifestations and anaphylactoid reactions have been reported [ see Adverse Reactions (6.2) ].
• Men with carcinoma of the breast or known or suspected carcinoma of the prostate gland [ see Warnings and Precautions (5.3) ].
• Women who are pregnant. Testosterone can cause virilization of the female fetus when administered to a pregnant woman [ see Use in Specific Populations (8.1) ].

5 WARNINGS AND PRECAUTIONS

5.1 Polycythemia

Increases in hematocrit levels, reflective of increases in red blood cell mass, may require discontinuation of AZMIRO. Check that hematocrit is not elevated prior to initiating AZMIRO. Periodically monitor hematocrit levels during treatment. If hematocrit becomes elevated, stop AZMIRO until hematocrit decreases to an acceptable concentration. If AZMIRO is restarted and again causes hematocrit to become elevated, stop AZMIRO permanently. An increase in red blood cell mass may increase the risk of thromboembolic events [ see Warnings and Precautions (5.2) ].

5.2 Venous Thromboembolism (VTE)

There have been postmarketing reports of venous thromboembolic events, including deep vein thrombosis (DVT) and pulmonary embolism (PE), in patients using testosterone replacement products, such as AZMIRO.
In the Testosterone Replacement therapy for Assessment of long-term Vascular Events and efficacy ResponSE in hypogonadal men (TRAVERSE) Study, a randomized, double-blind, placebo controlled, cardiovascular (CV) outcomes study, compared to placebo, topical testosterone gel was associated with a numerically higher incidence of VTE (1.7% vs 1.2%) which included DVT (0.6% vs 0.5%) and PE events (0.9% vs 0.5%) [see Adverse Reactions (6.1)].
Evaluate patients who report symptoms of pain, edema, warmth and erythema in the lower extremity for DVT and those who present with acute shortness of breath for PE. If a venous thromboembolic event is suspected, discontinue treatment with AZMIRO and initiate appropriate workup and management [see Adverse Reactions (6.2)].

5.3 Worsening of Benign Prostatic Hyperplasia (BPH) and Potential Risk of Prostate Cancer

• Patients with BPH treated with androgens are at an increased risk for worsening of signs and symptoms of BPH. Monitor patients with BPH for worsening signs and symptoms.
• Patients treated with androgens may be at increased risk for prostate cancer. Evaluate patients for prostate cancer prior to initiating and during treatment with androgens [ see Contraindications (4) ].

5.4 Blood Pressure Increases

Testosterone products, such as AZMIRO, can increase blood pressure. Blood pressure increases can increase cardiovascular (CV) risk over time.
The CV risk associated with topical testosterone gel was evaluated in TRAVERSE, randomized, double-blind, placebo-controlled, CV outcomes study in men with a history of CV disease or multiple CV risk factors. In TRAVERSE, topical testosterone gel increased mean systolic blood pressure by 1.0 mm Hg from baseline to 36 months, whereas a mean decrease from baseline of 0.5 mm Hg was observed in the placebo group at this timepoint, for a mean between-group difference of 1.5 mm Hg. However, the incidences of major adverse cardiovascular events (MACE), including cardiovascular death, non-fatal myocardial infarction [MI] and non-fatal stroke, were similar between treatment groups (7% for topical testosterone gel vs 7.3% for placebo) [See Adverse Reactions (6.1)].
Monitor blood pressure periodically in men using AZMIRO, especially men with hypertension. AZMIRO is not recommended for use in patients with uncontrolled hypertension.

5.5 Abuse of Testosterone and Monitoring of Serum Testosterone Concentrations

Testosterone has been subject to abuse, typically at doses higher than recommended for the approved indication and in combination with other anabolic androgenic steroids. Anabolic androgenic steroid abuse can lead to serious cardiovascular and psychiatric adverse reactions [ see Drug Abuse And Dependence (9) ].
If testosterone abuse is suspected, check serum testosterone concentrations to ensure they are within therapeutic range. However, testosterone levels may be in the normal or subnormal range in men abusing synthetic testosterone derivatives. Counsel patients concerning the serious adverse reactions associated with abuse of testosterone and anabolic androgenic steroids. Conversely, consider the possibility of testosterone and anabolic androgenic steroid abuse in suspected patients who present with serious cardiovascular or psychiatric adverse events.

5.6 Not for Use in Women

Due to lack of controlled studies in women and the potential for virilizing effects, AZMIRO is not indicated for use in women [ see Use in Specific Populations (8.1, 8.2) ].

5.7 Potential for Adverse Effects on Spermatogenesis

With large doses of exogenous androgens, including AZMIRO, spermatogenesis may be suppressed through feedback inhibition of pituitary follicle-stimulating hormone (FSH) possibly leading to adverse effects on semen parameters including sperm count [ see Use in Specific Populations (8.3) and Adverse Reactions (6.2) ]. Patients should be informed of this possible risk when deciding whether to use or to continue to use AZMIRO.

5.8 Hepatic Adverse Effects

Prolonged use of high doses of orally active 17-alpha-alkyl androgens (e.g., methyltestosterone) has been associated with serious hepatic adverse effects (peliosis hepatis, hepatic neoplasms, cholestatic hepatitis, and jaundice). Peliosis hepatis can be a life-threatening or fatal complication. Long-term therapy with intramuscular testosterone enanthate has produced multiple hepatic adenomas. AZMIRO is not a 17 alpha-alkyl androgen and is not known to produce hepatic adverse effects associated with 17-alpha-alkyl androgens.
Nonetheless, patients should be instructed to report any signs or symptoms of hepatic dysfunction (e.g., jaundice). If these occur, promptly discontinue AZMIRO while the cause is evaluated.

5.9 Edema

Androgens, including AZMIRO, may promote retention of sodium and water. Edema, with or without congestive heart failure, may be a serious complication in patients with pre-existing cardiac, renal or hepatic disease [ see Adverse Reactions (6.2) ]. In addition to discontinuation of the drug, appropriate work up and management of edema may be required.

5.10 Sleep Apnea

The treatment of hypogonadal men with testosterone products may potentiate sleep apnea in some patients, especially those with risk factors such as obesity or chronic lung diseases.

5.11 Gynecomastia

Gynecomastia may develop and occasionally persists in patients being treated for hypogonadism.

5.12 Lipid Changes

Changes in serum lipid profile may require dose adjustment of lipid lowering drugs or discontinuation of testosterone therapy. Monitor the lipid profile periodically after starting testosterone therapy.

5.13 Hypercalcemia

Androgens, including AZMIRO, should be used with caution in cancer patients at risk of hypercalcemia (and associated hypercalciuria). Monitor serum calcium concentrations periodically in these patients.

5.14 Decreased Thyroxine-binding Globulin

Androgens, including AZMIRO, may decrease concentrations of thyroxine-binding globulin, resulting in decreased total T 4 serum levels and increased resin uptake of T 3 and T 4. Free thyroid hormone levels remain unchanged, however, and there is no clinical evidence of thyroid dysfunction.

5.15 Increases in Prolactin

Increases in serum prolactin have been reported in patients treated with testosterone products, such as AZMIRO. Evaluate serum prolactin levels prior to initiating treatment with AZMIRO. Re-evaluate serum prolactin levels 3 to 4 months after starting treatment. If serum prolactin remains elevated, discontinue AZMIRO.

5.16 Adverse Effects on Bone Maturation

Testosterone use may result in acceleration of bone age and premature closure of epiphyses in pediatric patients. This adverse effect may result in compromised adult stature. The younger the pediatric patient the greater the risk of compromising final mature height. Monitor the effect on bone maturation by assessing bone age of the wrist and hand every 6 months.

6 ADVERSE REACTIONS

The following clinically significant adverse reactions are discussed elsewhere in the labeling:
• Polycythemia [ see Warnings and Precautions (5.1) ]
• Venous Thromboembolism [ see Warnings and Precautions (5.2)]
• Worsening of Benign Prostatic Hyperplasia (BPH) and Potential Risk of Prostate Cancer [ see Warnings and Precautions (5.3) ]
• Blood Pressure Increases [ see Warnings and Precautions (5.4) ]
• Hepatic Adverse Effects [ see Warnings and Precautions (5.8) ]
• Edema [ see Warnings and Precautions (5.9) ]
• Sleep Apnea [ see Warnings and Precautions (5.10) ]
• Gynecomastia [ see Warnings and Precautions (5.11) ]
• Lipid Changes [ see Warnings and Precautions (5.12) ]
• Hypercalcemia [ see Warnings and Precautions (5.13) ]
• Decreased Thyroxine-binding Globulin [ see Warnings and Precautions (5.14) ]
• Increases in Prolactin [ see Warnings and Precautions (5.15) ]
• Adverse Effects on Bone Maturation [ see Warnings and Precautions (5.16) ]

6.1 Clinical Trial Experience

Because clinical trials are conducted under widely varying conditions, adverse reaction rates observed in the clinical trials of a drug cannot be directly compared to rates in the clinical trials of another drug and may not reflect the rates observed in practice.
The safety of AZMIRO was evaluated, in Study 1, a randomized, single-dose, open-label study conducted in 27 adult males with hypogonadism. Patients were 18 to 65 years of age with a body mass index of 18 to 35 kg/m^2. Patients received a single intramuscular dose AZMIRO 200 mg or comparator intramuscular testosterone replacement therapy product and were observed for adverse reactions and injection site reactions over 31 days.
The most common adverse reactions in patients who received AZMIRO were injection site erythema (26%) and injection site reaction (4%). All cases of injection site erythema and injection site reaction were categorized as mild based on a pre-defined injection site assessment scale that defined injection site reactions as mild if they were slight or barely perceptible.

Cardiovascular Outcomes
TRAVERSE was a randomized, double-blind, cardiovascular outcomes study to assess the cardiovascular (CV) safety of topical testosterone gel compared to placebo in 5198 hypogonadal men aged 45 to 80 years with a history of CV disease or with multiple CV risk factors. The primary outcome was the incidence of the composite endpoint of major adverse cardiovascular events (MACE), consisting of CV death, non-fatal myocardial infarction (MI), and non-fatal stroke The mean duration of therapy was approximately 22 months. The mean duration of follow-up was 33 months. Approximately 61% of all patients discontinued topical testosterone gel or placebo therapy.
The mean patient age (±SD) was 63.3 (7.9) years, with 2452 patients aged 65 years or more (47%); 2847 (about 55%) patients had pre-existing cardiovascular disease, whereas 2357 patients (about 45%) had an elevated cardiovascular risk at baseline, and mean BMI was 35 kg/m^2. Approximately 80% of patients were White, 17% were Black, and 3% were of other races or ethnic groups. Approximately 69%, 84%, and 93% had diabetes mellitus, hyperlipidemia, and hypertension, respectively.
The mean serum testosterone concentration at baseline in patients receiving topical testosterone gel was 220.4 ng/dL (n=2596). The mean serum testosterone concentrations at 12 months, 24 months, 36 months, and 48 months in patients receiving topical testosterone gel were 440.5 ng/dL (n=1683), 420.9 ng/dl (n=1125), 428.7 ng/dL (n=731), and 365.2 ng/dL (n=220), respectively.
For patients treated with topical testosterone gel, the incidence of MACE was 7.0% (n=182 events) and for those receiving placebo, the incidence of MACE was 7.3% (n=190 events). The study demonstrated non-inferiority of topical testosterone gel versus placebo because the upper bound of 95% CI was less than the pre-specified risk margin, of 1.5 for MACE (Hazard Ratio 0.96 [95% CI: 0.78, 1.17]).
Additional Adverse Reactions Reported in TRAVERSE
Additional adverse reactions reported in TRAVERSE at an incidence rate >2% in either treatment group and greater in topical testosterone gel versus placebo included: nonfatal arrythmias warranting intervention (5.2% vs 3.3%), atrial fibrillation (3.5% vs 2.4%), acute kidney injury (2.3% vs 1.5%) and bone fracture (3.5% vs 2.5%). For the adverse reaction of bone fracture, each event was adjudicated by clinical review.

6.2 Other Adverse Reactions

The following adverse reactions associated with the use of testosterone were identified in clinical studies or postmarketing reports. Because some of these reactions were reported voluntarily from a population of uncertain size, it is not always possible to reliably estimate their frequency or establish a causal relationship to drug exposure.
Administration site reactions: Inflammation and pain at the site of intramuscular injection.
Allergic: Hypersensitivity, including skin manifestations and anaphylactoid reactions.
Cardiovascular disorders: myocardial infarction, stroke.
Endocrine and urogenital: Gynecomastia, premature closure of bony epiphyses with termination of growth, precocious puberty.
Fluid and electrolyte disturbances: Retention of sodium, chloride, water, potassium, calcium, and inorganic phosphates.
Gastrointestinal: Nausea, cholestatic jaundice, alterations in liver function tests, rarely hepatocellular neoplasms and peliosis hepatis.
Hematologic: Suppression of clotting factors II, V, VII, and X, bleeding in patients on concomitant anticoagulant therapy, and polycythemia.
Nervous system: Increased or decreased libido, headache, anxiety, depression, and generalized paresthesia.
Reproductive system: Excessive frequency and duration of penile erections, oligospermia, and priapism

Vascular disorders: Venous thromboembolism.

Skin and appendages: Male pattern baldness, seborrhea, and acne.
Special senses: Rare cases of central serous chorioretinopathy (CSCR).

7 DRUG INTERACTIONS

7.1 Insulin

Changes in insulin sensitivity or glycemic control may occur in patients treated with androgens. In diabetic patients, the metabolic effects of androgens may decrease blood glucose and, therefore, insulin requirements.

7.2 Oral Anticoagulants

Changes in anticoagulant activity may be seen with androgens. Frequent monitoring of INR and prothrombin time may be necessary in patients taking anticoagulants, especially at the initiation and termination of androgen therapy.

7.3 Corticosteroids

The concurrent use of testosterone with corticosteroids may result in increased fluid retention and should be monitored cautiously, particularly in patients with cardiac, renal or hepatic disease.

8 USE IN SPECIFIC POPULATIONS

8.1 Pregnancy

Risk Summary
AZMIRO is contraindicated in pregnant women and not indicated for use in females [see Contraindications (4)]. Testosterone is teratogenic and may cause fetal harm when administered to a pregnant woman based on data from animal studies (see Data) and its mechanism of action [ see Clinical Pharmacology (12.1) ]. Exposure of a female fetus to androgens may result in varying degrees of virilization. In animal developmental studies, exposure to testosterone in utero resulted in hormonal and behavioral changes in offspring and structural impairments of reproductive tissues in female and male offspring. These studies did not meet current standards for nonclinical development toxicity studies.
Data
Animal Data
In developmental studies conducted in rats, rabbits, pigs, sheep and rhesus monkeys, pregnant animals received intramuscular injection of testosterone during the period of organogenesis. Testosterone treatment at doses that were comparable to those used for testosterone replacement therapy resulted in structural impairments in both female and male offspring. Structural impairments observed in females included increased anogenital distance, phallus development, empty scrotum, no external vagina, intrauterine growth retardation, reduced ovarian reserve, and increased ovarian follicular recruitment. Structural impairments seen in male offspring included increased testicular weight, larger seminal tubular lumen diameter, and higher frequency of occluded tubule lumen. Increased pituitary weight was seen in both sexes.
Testosterone exposure in utero also resulted in hormonal and behavioral changes in offspring. Hypertension was observed in pregnant females and offspring in rats exposed to doses approximately twice those used for testosterone replacement therapy.

8.2 Lactation

Risk Summary
AZMIRO is not indicated for use in females.

8.3 Females and Males of Reproductive Potential

Infertility
Males
During treatment with large doses of exogenous androgens, including AZMIRO, spermatogenesis may be suppressed through feedback inhibition of the hypothalamic-pituitary-testicular-axis [ see Warnings and Precautions (5.7) ]. Reduced fertility is observed in some men taking testosterone replacement therapy. The impact on fertility may be irreversible. Testicular atrophy, subfertility, and infertility have also been reported in men who abuse anabolic androgenic steroids [ see Drug Abuse and Dependence (9.2) ].

8.4 Pediatric Use

Improper use may result in acceleration of bone age and premature closure of epiphyses. The effect on bone maturation should be monitored by assessing bone age of the wrist and hand every 6 months. In children, androgen treatment may accelerate bone maturation without producing compensatory gain in linear growth. This adverse effect may result in compromised adult stature. The younger the child the greater the risk of compromising final mature height. Precocious puberty has also been reported with use of testosterone.
The safety and effectiveness of AZMIRO have not been established in pediatric patients young than 12 years of age.

8.5 Geriatric Use

Geriatric patients treated with androgens may be at an increased risk of developing BPH and prostatic carcinoma [see Warnings and Precautions (5.3)].

9 DRUG ABUSE AND DEPENDENCE

9.1 Controlled Substance

AZMIRO contains testosterone, a Schedule III controlled substance.

9.2 Abuse

Drug abuse is intentional non-therapeutic use of a drug, even once, for its rewarding psychological and physiological effects. Abuse and misuse of testosterone are seen in male and female adults and adolescents. Testosterone, often in combination with other anabolic androgenic steroids (AAS), and not obtained by prescription through a pharmacy, may be abused by athletes and bodybuilders. There have been reports of misuse by men taking higher doses of legally obtained testosterone than prescribed and continuing testosterone despite adverse events or against medical advice.
Abuse-Related Adverse Reactions
Serious adverse reactions have been reported in individuals who abuse anabolic androgenic steroids, and include cardiac arrest, myocardial infarction, hypertrophic cardiomyopathy, congestive heart failure, cerebrovascular accident, hepatotoxicity, and serious psychiatric manifestations, including major depression, mania, paranoia, psychosis, delusions, hallucinations, hostility, and aggression.
The following adverse reactions have also been reported in men: transient ischemic attacks, convulsions, hypomania, irritability, dyslipidemias, testicular atrophy, subfertility, and infertility.
The following additional adverse reactions have been reported in women: hirsutism, virilization, deepening of voice, clitoral enlargement, breast atrophy, male-pattern baldness, and menstrual irregularities.
The following adverse reactions have been reported in male and female adolescents: premature closure of bony epiphyses with termination of growth, and precocious puberty.
Because these reactions are reported voluntarily from a population of uncertain size and may include abuse of other agents, it is not always possible to reliably estimate their frequency or establish a causal relationship to drug exposure.

9.3 Dependence

Behaviors Associated with Addiction
Continued abuse of testosterone and other anabolic steroids, leading to addiction is characterized by the following behaviors:
• Taking greater dosages than prescribed
• Continued drug use despite medical and social problems due to drug use
• Spending significant time to obtain the drug when supplies of the drug are interrupted
• Giving a higher priority to drug use than other obligations
• Having difficulty in discontinuing the drug despite desires and attempts to do so
• Experiencing withdrawal symptoms upon abrupt discontinuation of use

Physical dependence is characterized by withdrawal symptoms after abrupt drug discontinuation or a significant dose reduction of a drug. Individuals taking supratherapeutic doses of testosterone may experience withdrawal symptoms lasting for weeks or months which include depressed mood, major depression, fatigue, craving, restlessness, irritability, anorexia, insomnia, decreased libido and hypogonadotropic hypogonadism.
Drug dependence in individuals using approved doses of testosterone for approved indications has not been documented.

10 OVERDOSAGE

There is one report of acute overdosage with use of an approved injectable testosterone product: this subject had serum testosterone levels of up to 11,400 ng/dL with a cerebrovascular accident. Treatment of overdosage consists of discontinuation of AZMIRO and appropriate symptomatic and supportive care.

11 DESCRIPTION

AZMIRO (testosterone cypionate) injection for intramuscular injection, contains testosterone cypionate which is the oil-soluble 17 (beta)-cyclopentylpropionate ester of the androgenic hormone testosterone.
Testosterone cypionate is a white or creamy white crystalline powder, odorless or nearly so and stable in air. It is insoluble in water, freely soluble in alcohol, chloroform, dioxane, ether, and soluble in vegetable oils.
The chemical name for testosterone cypionate is androst-4-en-3-one, 17-(3-cyclopentyl-1-oxopropoxy)-, (17ß)-. Its molecular formula is C 27H 40O 3, and the molecular weight 412.61. The structural formula is shown in the following figure:

AZMIRO (testosterone cypionate) injection is provided as sterile, clear colorless to pale yellow solution containing 200 mg/mL testosterone cypionate in vials and prefilled syringes.

Each mL of solution contains:
Testosterone cypionate………………………………………..200 mg
Benzyl alcohol………………………………………………….20 mg
Benzyl benzoate……………………………………………….0.2 mL
Cottonseed oil…………………………………………………542 mg

12 CLINICAL PHARMACOLOGY

12.1 Mechanism of Action

Endogenous androgens, including testosterone and dihydrotestosterone (DHT), are responsible for normal growth and development of the male sex organs and for maintenance of secondary sex characteristics. These effects include growth and maturation of the prostate, seminal vesicles, penis, and scrotum; the development of male hair distribution, such as facial, pubic, chest, and axillary hair; laryngeal enlargement, vocal cord thickening, alterations in body musculature and fat distribution.
Male hypogonadism, a clinical syndrome resulting from insufficient secretion of testosterone, has two main etiologies. Primary hypogonadism is caused by defects of the gonads, such as Klinefelter's Syndrome or Leydig cell aplasia, whereas secondary hypogonadism is the failure of the hypothalamus (or pituitary) to produce sufficient gonadotropins (FSH, LH).

12.2 Pharmacodynamics

The exposure-response relationship and time course of pharmacodynamic response for the safety and effectiveness of testosterone have not been fully characterized.

12.3 Pharmacokinetics

Absorption
Testosterone esters are less polar than free testosterone. Testosterone esters in oil injected intramuscularly are absorbed slowly from the lipid phase; thus, AZMIRO can be given at intervals of two to four weeks.
Pharmacokinetic parameters of baseline-corrected testosterone obtained following a single-dose intramuscular administration of AZMIRO 200 mg in prefilled syringe in 26 hypogonadal adult males are summarized in Table 1 below.

Table 1: Mean (±SD) Baseline-corrected Testosterone Pharmacokinetic Parameters

Following a Single-dose Intramuscular Administration of AZMIRO 200 mg in Hypogonadal Males (N=26)

Parameter | Mean (±SD)
AUC 0-t(hr·ng/dL) | 137218.7 (±62360.0)
C max(ng/dL) | 758.0 (±288.7)
T max(hr) | 71.7 (24.0, 191.0) a

aReported in median (min, max).

Distribution
Circulating testosterone is primarily bound in serum to sex hormone-binding globulin (SHBG) and albumin. Approximately 40% of testosterone in plasma is bound to SHBG, 2% remains unbound (free) and the rest is bound to albumin and other proteins.
Elimination
The half-life of AZMIRO when injected intramuscularly is approximately eight days.
Metabolism
Inactivation of testosterone occurs primarily in the liver. Testosterone is metabolized to various 17-keto steroids through two different pathways. The major active metabolites of testosterone are dihydrotestosterone (DHT) and estradiol.
Excretion
About 90 percent of a dose of testosterone is excreted in the urine as glucuronic and sulfuric acid conjugates of testosterone and its metabolites. About 6 percent of a dose is excreted in the feces, mostly in the unconjugated form.

13 NONCLINICAL TOXICOLOGY

13.1 Carcinogenesis, Mutagenesis, Impairment of Fertility

Carcinogenesis
Testosterone has been tested by subcutaneous injection and implantation in mice and rats. The implant induced cervical-uterine tumors in mice, which metastasized in some cases.
There is suggestive evidence that injection of testosterone into some strains of female mice increases their susceptibility to hepatoma. Testosterone is also known to increase the number of tumors and decrease the degree of differentiation of chemically induced carcinomas of the liver in rats.

Mutagenicity
Testosterone was negative in the in vitro Ames and in the in vivo mouse micronucleus assays.
Impairment of Fertility
The administration of exogenous testosterone suppresses spermatogenesis in the rat, dog and non-human primates, which was reversible on cessation of the treatment.

16 HOW SUPPLIED/STORAGE AND HANDLING

AZMIRO (testosterone cypionate) injection is supplied as a sterile, clear colorless to pale yellow solution in single-dose vials and single-dose prefilled syringes as 200 mg/mL testosterone cypionate.

NDC Number | Package Size
24338-056-01 | 1 mL vials
24338-055-01 | 1 mL prefilled syringes

Store at 15°C to 25°C (59°F to 77°F); excursions permitted to 2°C to 30°C (36°F to 86°F). Store product in carton to protect contents from light.

17 PATIENT COUNSELING INFORMATION

Polycythemia
Advise patients that AZMIRO can cause an increase in hematocrit levels that may increase the risk of thromboembolic events. Advise patients about the importance of completing laboratory testing as instructed by their health care provider while on AZMIRO [ see Warnings and Precautions (5.1) ].

Venous Thromboembolism
Advise patients that AZMIRO can cause venous thromboembolism. Advise patients of the signs and symptoms of venous thromboembolism, which may include the following: lower limb pain, edema, or erythema; and dyspnea or chest pain. Advise patients to promptly report the signs and symptoms of venous thromboembolism, discontinue use of AZMIRO, and seek urgent medical care.

Increase in Blood Pressure
Advise patients that AZMIRO can increase BP which can increase cardiovascular risk over time. Instruct patients about the importance of monitoring BP periodically while on AZMIRO. If BP increases while on AZMIRO, antihypertensive medications may need to be started, added, or adjusted to control BP, or AZMIRO may need to be discontinued.

Worsening of Benign Prostatic Hyperplasia (BPH) and Potential Risk of Prostate Cancer
Advise patients that AZMIRO can cause increased symptoms of BPH and can increase the risk for prostate cancer. Advise patients to contact their health care provider if they have any prostate-related symptoms [ see Warnings and Precautions (5.3) ].
Edema
Advise patients with preexisting cardiac, renal, or hepatic disease that AZMIRO can cause edema. Advise patients to notify their health care provider if edema develops or worsens [ see Warnings and Precautions (5.9) ].
Sleep Apnea
Advise patients that AZMIRO can worsen sleep apnea especially in patients with risk factors such as obesity or chronic lung diseases [ see Warnings and Precautions (5.10) ].
Gynecomastia
Advise patients that AZMIRO can cause gynecomastia [ see Warnings and Precautions (5.11) ].
Manufactured for:
Azurity Pharmaceuticals, Inc.
Woburn, MA 01801
Manufactured by:
LSNE-LEON SLU
Calle nicostrato vela
(pq. Tecchnologico leon),
S/N – M1.1-M1.2, Leon, 24009,
Spain (ESP)
Patent: https://azurity.com/patents_and_trademarks/
This product's labeling may have been updated. For current Full Prescribing Information, please visit www.azmiro.com
AZM-PI-01 Rev. JULY2025

MEDICATION GUIDE

AZMIRO TM (AZ-MEER-OH)
(testosterone cypionate)
injection, for intramuscular use, CIII

What is the most important information I should know about AZMIRO?
AZMIRO can cause serious side effects, including:
• Increase in red blood cell counts (hematocrit) or hemoglobin.
o AZMIRO increases red blood cell counts in some people. High red blood cell counts increase the risk of blood clots, strokes, and heart attacks.
o You may need to stop AZMIRO if your red blood cell count increases.
o Your healthcare provider should check your red blood cell count and hemoglobin while you receive AZMIRO.

What is AZMIRO?
AZMIRO is a prescription medicine that contains testosterone. AZMIRO is used to treat adult men who have low or no testosterone due to certain medical conditions.
• It is not known if AZMIRO is safe or effective to treat men who have low testosterone due to aging.
• It is not known if AZMIRO is safe or effective in children younger than 12 years old. Improper use of testosterone may affect bone growth in children.
• AZMIRO is a controlled substance (CIII) because it contains testosterone that can be a target for people who abuse prescription medicines. Selling or giving away this medicine may harm others and it is against the law.
• AZMIRO is not meant for use in women.

Do not receive AZMIRO if you:
• are allergic to AZMIRO or to any ingredients in AZMIRO. See the end of this Medication Guide for a complete list of ingredients in AZMIRO.
• have breast cancer.
• have or might have prostate cancer.
• are a woman who is pregnant. AZMIRO may harm your unborn baby.

What should I tell my healthcare provider before receiving AZMIRO?
Before receiving AZMIRO, tell your healthcare provider about all of your medical conditions including if you:
• have high red blood cell count (hematocrit) or high hemoglobin laboratory value.
• have breast cancer.
• have or might have prostate cancer.
• have urinary problems due to an enlarged prostate.
• have high blood pressure or are being treated for high blood pressure.
• have heart problems.
• have liver or kidney problems.
• have problems breathing while you sleep (sleep apnea).
Tell your healthcare provider about all the medicines you take, including prescription and over-the-counter medicines, vitamins, and herbal supplements. Using AZMIRO with certain other medicines can affect each other. Especially, tell your healthcare provider if you take:
• insulin.
• medicines that decrease blood clotting (blood thinners).
• corticosteroids.
Ask your healthcare provider or pharmacist for a list of these medicines, if you are not sure. Know the medicines you take. Keep a list of your medicines and show them to your healthcare provider and pharmacist when you get a new medicine.

How will I receive AZMIRO?
• Your healthcare provider will inject AZMIRO deep into the muscle of your buttock.
• Your healthcare provider will test your blood before you receive and while you are receiving AZMIRO.

What are the possible side effects of AZMIRO?
AZMIRO may cause serious side effects including:
See “What is the most important information I should know about AZMIRO?”
• If you already have an enlarged prostate, your signs and symptoms may worsen while receiving AZMIRO. This may include:
o increased urination at night.
o trouble starting your urine stream.
o urinating many times during the day.
o urge to go to the bathroom right away.
o a urine accident.
o inability to pass urine or weak urine flow.
• Increased risk of prostate cancer. Your healthcare provider should check you for prostate cancer or any other prostate problems before you start and while you receive AZMIRO.
• Blood clots in the legs or lungs. Signs and symptoms of a blood clot in your leg can include leg pain, swelling or redness. Signs and symptoms of a blood clot in your lungs can include difficulty breathing or chest pain.
• Increased blood pressure. AZMIRO can increase your blood pressure, which can increase your risk of having a heart attack or stroke over time. Your risk may be greater if you have already had a heart attack or stroke or if you have other risk factors for heart attack or stroke. You may need to start new medicines or have medicines changed for high blood pressure while on AZMIRO. If your blood pressure cannot be controlled, AZMIRO may need to be stopped. Your healthcare provider should check your blood pressure while you use AZMIRO.
• Abuse. Testosterone can be abused, when taken at higher than prescribed doses and when used with other anabolic steroids. Abuse can cause serious heart and psychological side effects. Your healthcare provider should check you for signs of abuse before and during treatment with AZMIRO.
• AZMIRO may lower your sperm count.
• Liver problems. Symptoms of liver problems may include:
o nausea or vomiting.
o yellowing of your skin or whites of your eyes.
o dark urine.
o pain on the right side of your stomach area (abdominal pain).
• Swelling of your ankles, feet, or body (edema), with or without heart failure. This may cause serious problems for people who have heart, kidney or liver disease.
• Breathing problems while you sleep (sleep apnea).
• Enlarged or painful breasts.
• Changes in certain blood tests. These changes include changes in liver tests, increased calcium, decreased thyroid hormones, and increased prolactin hormones (hormone made by pituitary gland) levels.
• Increased risk in children of bone growth problems. AZMIRO may affect a child’s final adult height (stature). The child’s bone growth should be checked every 6 months while they are receiving AZMIRO.
Call your healthcare provider right away if you have any of the serious side effects listed above.
The most common side effects of AZMIRO include:
• injection site reactions including: bruising, bleeding, redness, hardness.
• increased red blood cell count.
• enlarged or painful breasts.
• headache.
• depression.
Other side effects include more erections than are normal for you or erections that last a long time. Tell your healthcare provider if you have any side effect that bothers you or that does not go away.
These are not all the possible side effects of AZMIRO. For more information, ask your healthcare provider or pharmacist.
Call your doctor for medical advice about side effects. You may report side effects to FDA at 1-800-FDA-1088.

General information about the safe and effective use of AZMIRO.
Medicines are sometimes prescribed for purposes other than those listed in a Medication Guide. You can ask your pharmacist or healthcare provider for information about AZMIRO that is written for healthcare professionals.

What are the ingredients in AZMIRO?
Active ingredient: testosterone
Inactive ingredients: benzyl alcohol, benzyl benzoate and cottonseed oil.
Manufactured for:
Azurity Pharmaceuticals, Inc.
Woburn, MA 01801
Manufactured by:
LSNE-LEON SLU
Calle nicostrato vela
(pq. Tecchnologico leon),
S/N – M1.1-M1.2, Leon, 24009,
Spain (ESP)
Patent: https://azurity.com/patents_and_trademarks/
This Medication Guide may have been updated. For current Medication Guide Information, please visit www.azmiro.com
AZM-MG-01 Rev. JULY2025

PACKAGE LABEL.PRINCIPAL DISPLAY PANEL

200 MG/ML - VIAL LABEL

NDC 24338-056-01
1 mL Single-Dose Vial
AZMIRO (testosterone cypionate) injection, USP
CIII

For intramuscular use only
Rx only

Principal Display Panel - 200 MG/ML - VIAL CARTON
NDC 24338-056-01
1 mL Single-Dose Vial
AZMIRO (testosterone cypionate) injection, USP
CIII
For intramuscular use only
Rx only

200 MG/ML - PREFILLED SYRINGE LABEL

NDC 24338-055-01
1 mL Single-dose Prefilled Syringe
AZMIRO (testosterone cypionate) injection, USP
CIII
For intramuscular use only
Rx only

Principal Display Panel - 200 MG/ML - PREFILLED SYRINGE CARTON
NDC 24338-055-01
1 mL Single-dose Prefilled Syringe
AZMIRO (testosterone cypionate) injection, USP
CIII
For intramuscular use only
Rx only